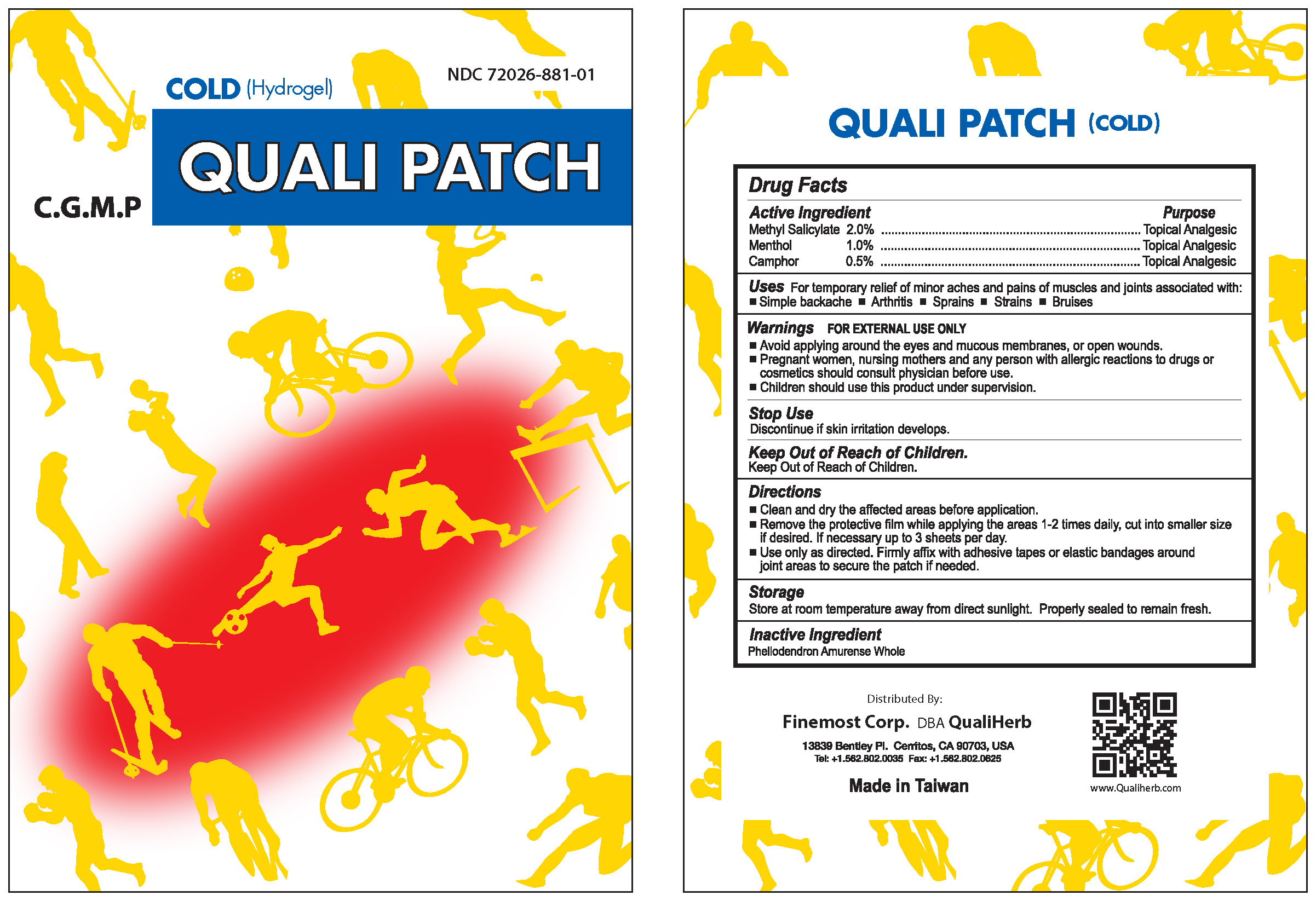 DRUG LABEL: Quali Patch (Cold)
NDC: 72026-881 | Form: PATCH
Manufacturer: Finemost Corporation
Category: otc | Type: HUMAN OTC DRUG LABEL
Date: 20230601

ACTIVE INGREDIENTS: METHYL SALICYLATE 2 g/100 g; MENTHOL 1 g/100 g; CAMPHOR (SYNTHETIC) 0.5 g/100 g
INACTIVE INGREDIENTS: PHELLODENDRON AMURENSE WHOLE

Finemost Corporation

ACTIVE INGREDIENTS

Methyl Salicylate 2.0%

Menthol 1.0%

Camphor 0.5%

Purpose

Methyl Salicylate Topical Analgesic

Menthol Topical Analgesic

Camphor Topical Analgesic

Uses

For temporary relief of minor aches and pains of muscles and joints associated with:

Simple backache
Arthritis
Sprains
Strains
Bruises

Warnings

1. For external use only. Avoid applying around the eyes and mucous membranes, or open wounds.
2. Pregnant women, nursing mothers and any person with allergic reactions to drugs or cosmetics should consult physician before use. Children should use this product under supervision.

Stop Use

Discontinue if skin irritation develops.

Keep Out of Reach Of Children.

Directions

1. Clean and dry the affected areas before application.
2. Remove the protective film while applying the areas 1-2 times daily, cut into smaller size if desired. If necessary up to 3 sheets per day.
3. Use only as directed. Firmly affix with adhesive tapes or elastic bandages around joint areas to secure the patch if needed.

Storage

Store at room temperature away from direct sunlight. Properly sealed to remain fresh.

Inactive Ingredients

Phellodendron Amurense Whole

Distributed by

Finemost Corp. DBA QualiHerb

Cerritos, Ca 90703

Tel: (562)802-0035

Fax: (562)802-0625

Made in Taiwan